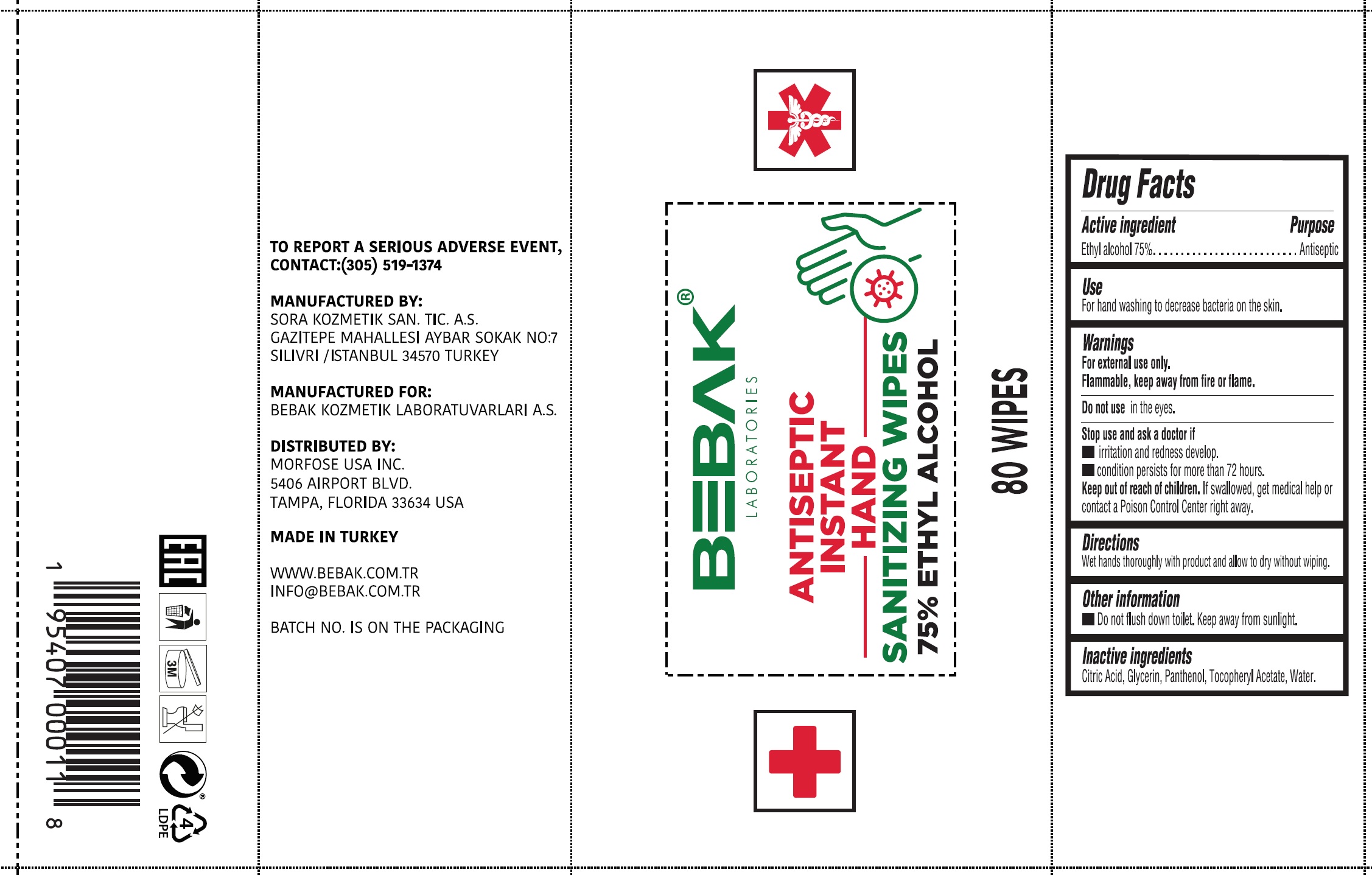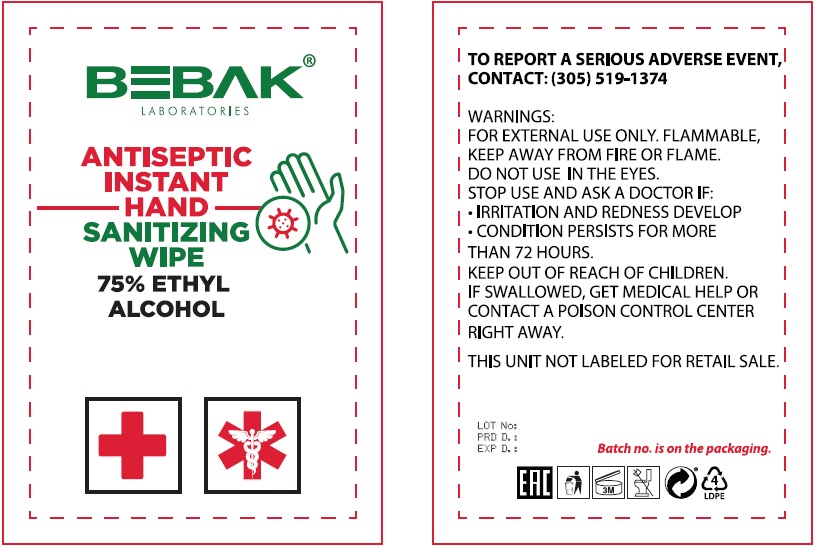 DRUG LABEL: Hygienic Instant Hand Sanitizing Wipes
NDC: 77462-010 | Form: CLOTH
Manufacturer: SORA KOZMETIK SANAYI TICARET ANONIM SIRKETI
Category: otc | Type: HUMAN OTC DRUG LABEL
Date: 20231028

ACTIVE INGREDIENTS: ALCOHOL 0.75 mL/1 mL
INACTIVE INGREDIENTS: CITRIC ACID MONOHYDRATE; GLYCERIN; PANTHENOL; .ALPHA.-TOCOPHEROL ACETATE; WATER

Hygienic Instant Hand Sanitizing Wipes

Active ingredient

Ethyl alcohol 75%

Purpose

Antiseptic

Use

For hand washing to decrease bacteria on the skin.

Warnings

For external use only.

Flammable, keep away from fire or flame.

Do not use

in the eyes.

Stop use and ask a doctor if

irritation and redness develop.

condition persists for more than 72 hours.

Keep out of reach of children.

If swallowed, get medical help or contact a Poison Control Center right away.

Directions

Wet hands thoroughly with product and allow to dry without wiping.

Other information

Do not flush down toilet, Keep away from sunlight.

Inactive ingredients

Citric Acid, Glycerin, Panthenol, Tocopheryl Acetate, Water.